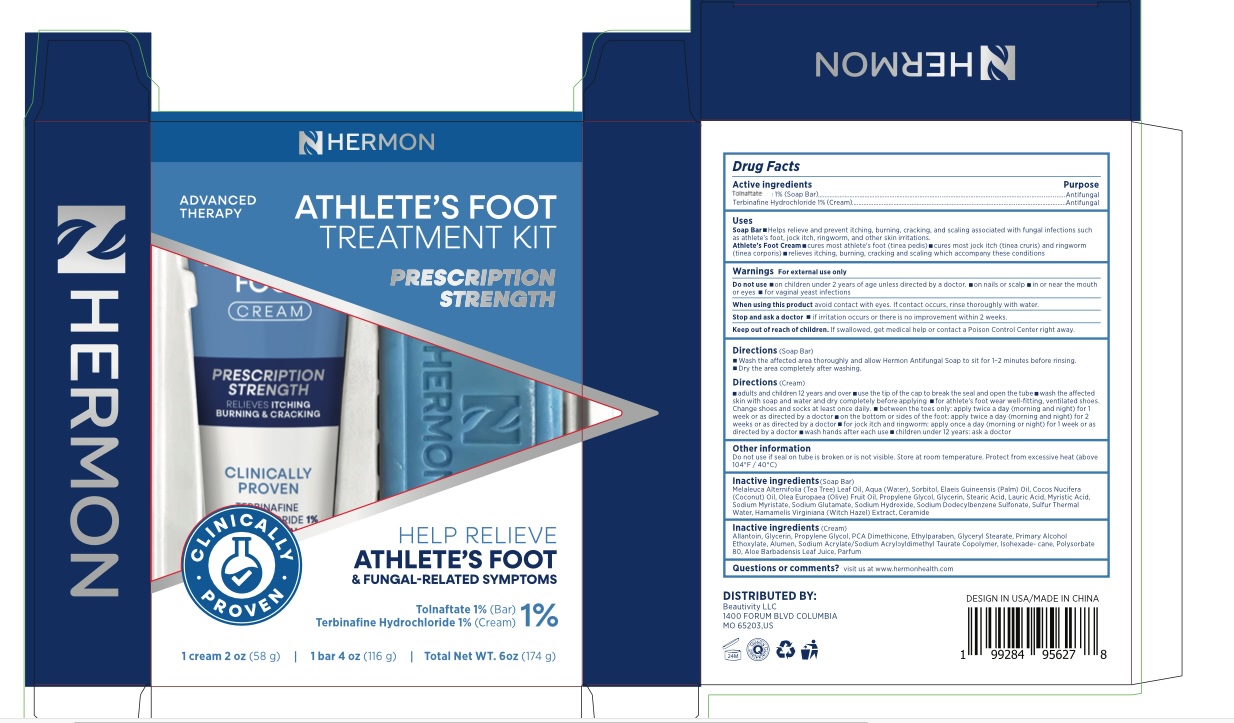 DRUG LABEL: Athlete Foot Treatment Kit
NDC: 85398-008 | Form: KIT | Route: TOPICAL
Manufacturer: Beautivity LLC
Category: otc | Type: HUMAN OTC DRUG LABEL
Date: 20260302

ACTIVE INGREDIENTS: TERBINAFINE HYDROCHLORIDE 1 g/100 g; TOLNAFTATE 1 g/100 g
INACTIVE INGREDIENTS: POTASSIUM ALUM; PROPYLENE GLYCOL; ALOE BARBADENSIS LEAF JUICE; ALLANTOIN; POLYSORBATE 80; DIMETHICONE; C12-15 PARETH-7; ISOHEXADECANE; GLYCERIN; ETHYLPARABEN; SODIUM ACRYLATE/SODIUM ACRYLOYLDIMETHYLTAURATE COPOLYMER (4000000 MW); GLYCERYL STEARATE; SODIUM GLUTAMATE; SORBITOL; HAMAMELIS VIRGINIANA BARK; SODIUM DODECYLBENZENESULFONATE; COCOS NUCIFERA (COCONUT) OIL; SODIUM HYDROXIDE; GLYCERIN; ELAEIS GUINEENSIS (PALM) OIL; WATER; SODIUM MYRISTATE; SULFUR; PROPYLENE GLYCOL; STEARIC ACID; MELALEUCA ALTERNIFOLIA (TEA TREE) LEAF OIL; MYRISTIC ACID; OLEA EUROPAEA (OLIVE) FRUIT OIL; LAURIC ACID

Update-85398-008-01

ACTIVE INGREDIENT

Tolnaftate 1% (Soap Bar)

Terbinafine Hydrochloride 1% (Cream)

PURPOSE

antifungal

INDICATIONS AND USAGE

Soap Bar

- Helps relieve and prevent itching, burning, cracking, and scaling associated with fungal infections such as athlete's foot, jock itch, ringworm, and other skin irritations.

Cream

- Cures most athlete's foot (tinea pedis)
- Cures most jock itch (tinea cruris) and ringworm (tinea corporis)
- Relieves itching, burning, cracking and scaling which accompany these conditions

WARNINGS

For external use only

DO NOT USE

- on children under 2 years of age unless directed by a doctor
- on nails and scalp
- in or near the mouth or eyes
- for vaginal yeast infections

When using this product avoid contact with eyes. If contact occurs, rinse thoroughly with water.

Stop use and ask a doctor

- If irritatioin occurs or there is no improvement within 2 weeks.

KEEP OUT OF REACH OF CHILDREN

If swallowed, get medical help or contact a Poison Control Center right away.

DOSAGE AND ADMINISTRATION

Soap Bar

- Wash the affected area thoroughly
- Allow Hermon Antifungal Soap to sit for 1-2 minutes before rinsing.
- Dry the area completely after washing.

Cream

- adults and children 12 years and over
- use the tip of the cap to break the seal and open the tube
- wash the affected skin with soap and water and dry completely before applying
- for athlete's foot wear well-fitting, ventilated shoes. Change shoes and socks at least once daily.
- between the toes only: apply twice a day (morning and night) for 1 week or as directed by a doctor
- on the bottom or sides of the foot: apply twice a day (morning and night) for 2 weeks or as directed by a doctor
- for jock itch and ringworm: apply once a day (morning or night) for 1 week or as directed by a doctor
- wash hands after each use
- children under 12 years: ask a doctor

Do not use if seal on tube is broken or is not visible. Store at room temperature. Protect from excessive heat (above 104°F / 40°C)

INACTIVE INGREDIENT

Soap Bar
Melaleuca Alternifolia (Tea Tree) Leaf Oil, Aqua (Water), Sorbitol, Elaeis Guineensis (Palm) Oil, Cocos Nucifera (Coconut) Oil, Olea Europaea (Olive) Fruit Oil, Propylene Glycol, Glycerin, Stearic Acid, Lauric Acid, Myristic Acid, Sodium Myristate, Sodium Glutamate, Sodium Hydroxide, Sodium Dodecylbenzene Sulfonate, Sulfur Thermal Water, Hamamelis Virginiana (Witch Hazel) Extract, Ceramide

Inactive ingredients
Cream
Allantoin, Glycerin, Propylene Glycol, PCA Dimethicone, Ethylparaben, Glyceryl Stearate, Primary Alcohol Ethoxylate, Alumen, Sodium Acrylate/Sodium Acryloyldimethyl Taurate Copolymer, Isohexade- cane, Polysorbate 80, Aloe Barbadensis Leaf Juice, Parfum

QUESTIONS

visit us at www.hermonhealth.com